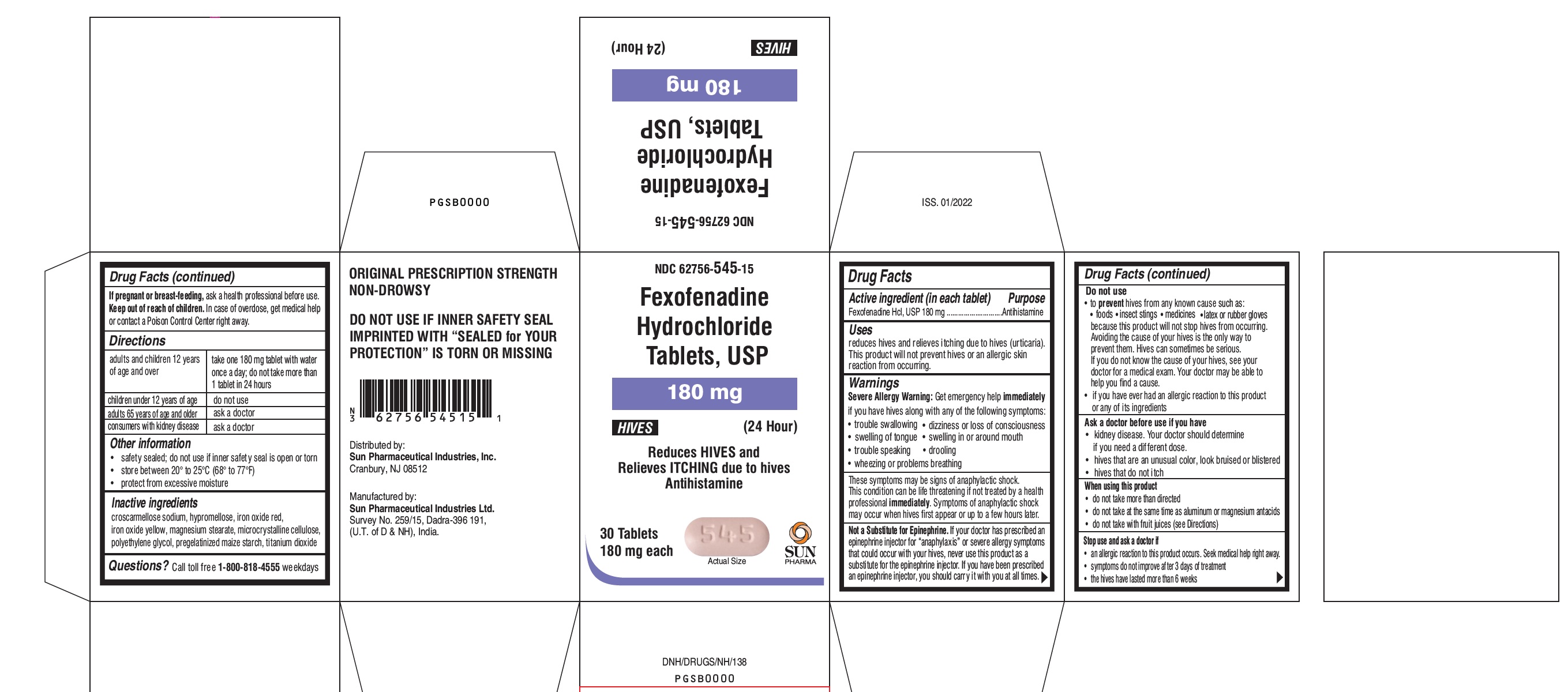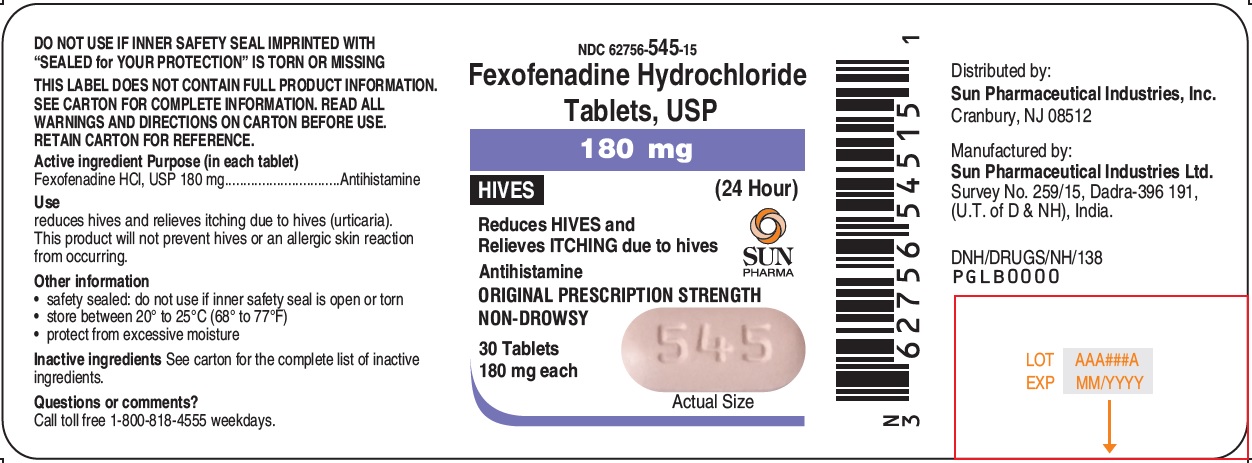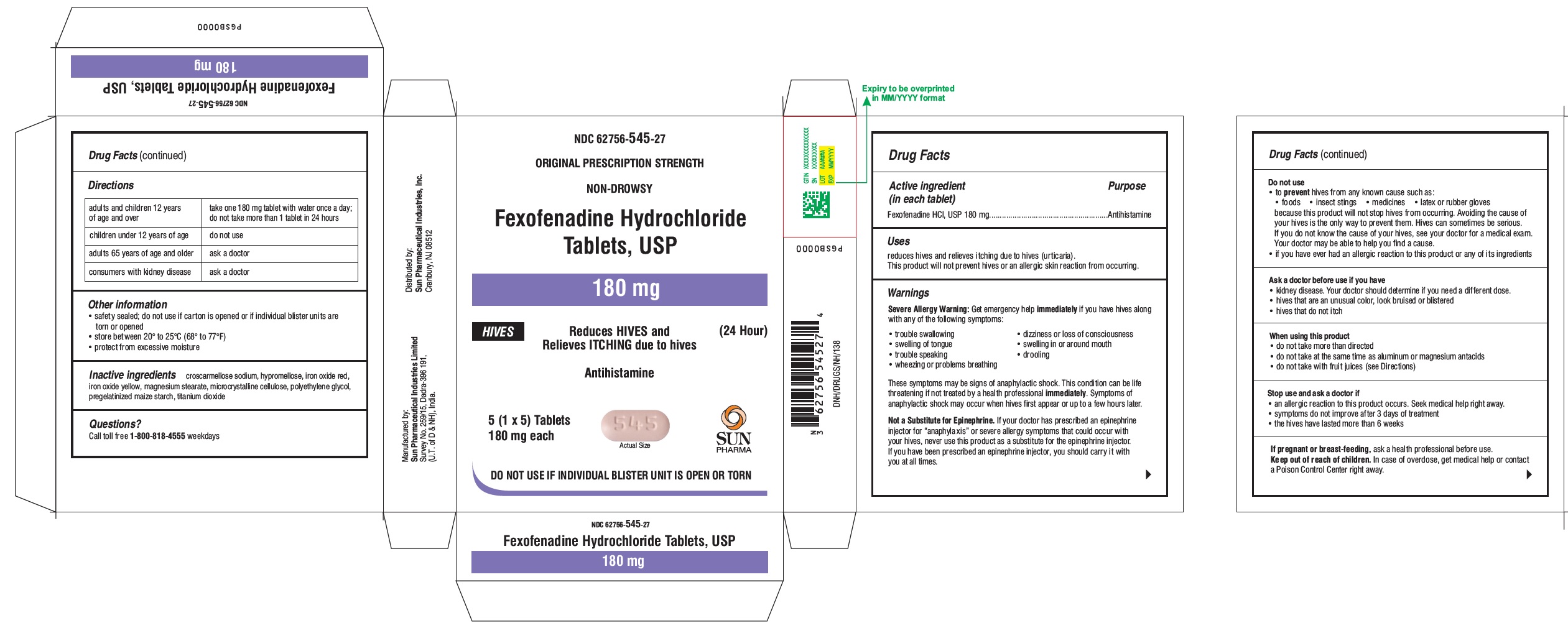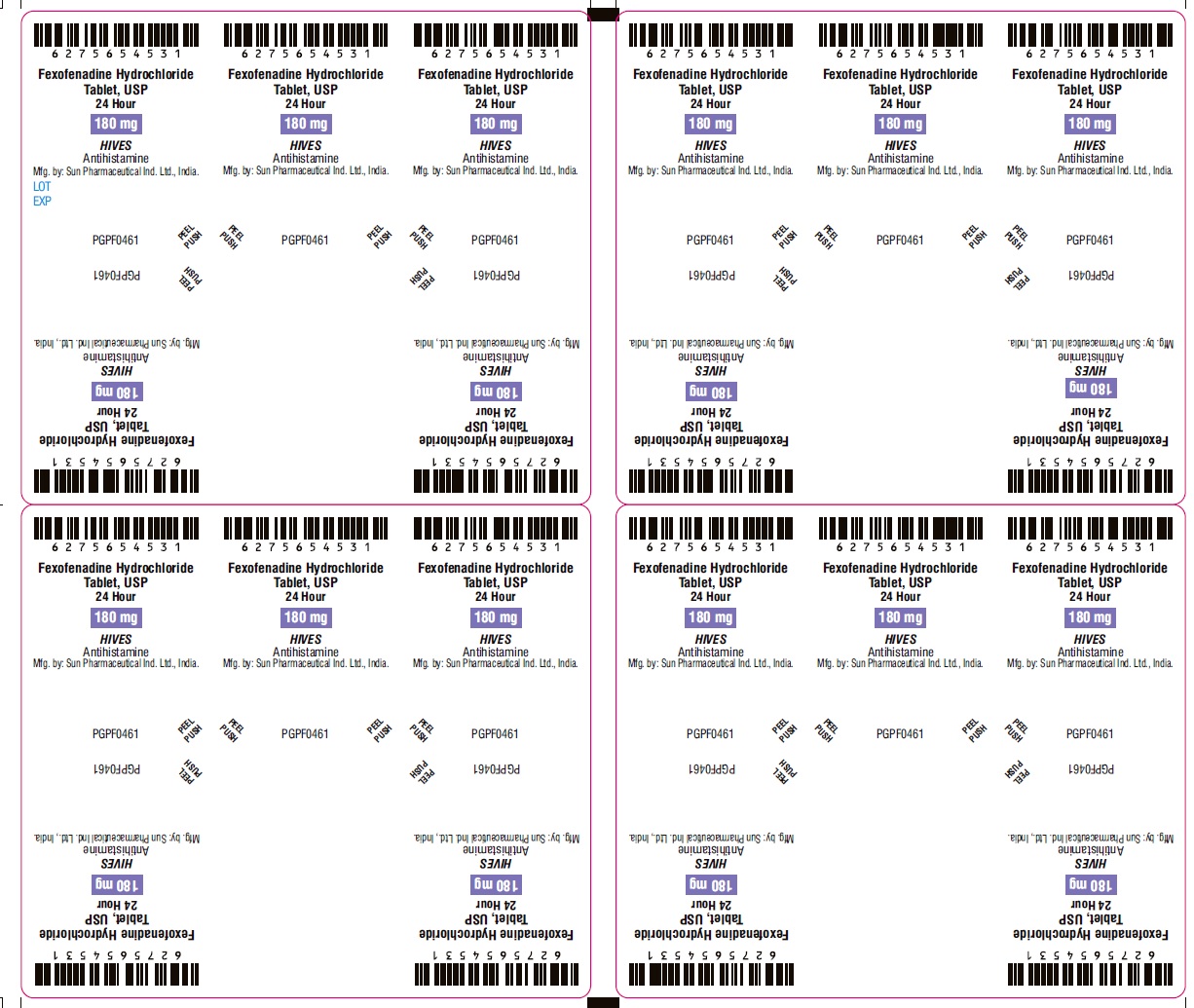 DRUG LABEL: FEXOFENADINE HYDROCHLORIDE
NDC: 62756-545 | Form: TABLET, FILM COATED
Manufacturer: Sun Pharmaceutical Industries, Inc.
Category: otc | Type: Human OTC Drug Label
Date: 20220627

ACTIVE INGREDIENTS: FEXOFENADINE HYDROCHLORIDE 180 mg/1 1
INACTIVE INGREDIENTS: MICROCRYSTALLINE CELLULOSE; STARCH, CORN; CROSCARMELLOSE SODIUM; MAGNESIUM STEARATE; HYPROMELLOSE 2910 (6 MPA.S); TITANIUM DIOXIDE; POLYETHYLENE GLYCOL 400; FERRIC OXIDE RED; FERRIC OXIDE YELLOW

Fexofenadine Hydrochloride Tablets, USP

Active ingredient (in each tablet)

For 180 mg:
Fexofenadine HCl, USP 180 mg

Purpose

Antihistamine

Uses

reduces hives and relieves itching due to hives (urticaria). This product will not prevent hives or an allergic skin reaction from occurring.

Warnings

Severe Allergy Warning: Get emergency help immediately if you have hives along with any of the following symptoms:

- trouble swallowing
- dizziness or loss of consciousness
- swelling of tongue
- swelling in or around mouth
- trouble speaking
- drooling
- wheezing or problems breathing

These symptoms may be signs of anaphylactic shock. This condition can be life threatening if not treated by a health professional immediately. Symptoms of anaphylactic shock may occur when hives first appear or up to a few hours later.
Not a Substitute for Epinephrine. If your doctor has prescribed an epinephrine injector for “anaphylaxis” or severe allergy symptoms that could occur with your hives, never use this product as a substitute for the epinephrine injector. If you have been prescribed an epinephrine injector, you should carry it with you at all times.

Do not use

- to prevent hives from any known cause such as:
  - foods
  - insect stings
  - medicines
  - latex or rubber gloves because this product will not stop hives from occurring. Avoiding the cause of your hives is the only way to prevent them. Hives can sometimes be serious. If you do not know the cause of your hives, see your doctor for a medical exam. Your doctor may be able to help you find a cause.
- if you have ever had an allergic reaction to this product or any of its ingredients

Ask a doctor before use if you have

- kidney disease. Your doctor should determine if you need a different dose.
- hives that are an unusual color, look bruised or blistered
- hives that do not itch

When using this product

- do not take more than directed
- do not take at the same time as aluminum or magnesium antacids
- do not take with fruit juices (see Directions)

Stop use and ask doctor if

- an allergic reaction to this product occurs. Seek medical help right away.
- symptoms do not improve after 3 days of treatment
- the hives have lasted more than 6 weeks

If pregnant or breast-feeding

ask a health professional before use.

Keep out of reach of children.

In case of overdose, get medical help or contact a Poison Control Center right away.

Directions

For 180 mg:

adults and children 12 years of age and over | take one 180 mg tablet with water once a day; do not take more than 1 tablet in 24 hours
children under 12 years of age | do not use
adults 65 years of age and older | ask a doctor
consumers with kidney disease | ask a doctor

Other information

- safety sealed; do not use if inner safety seal is open or torn
- store between 20° to 25°C (68° to 77°F)
- protect from excessive moisture

Inactive ingredients

croscarmellose sodium, hypromellose, iron oxide red, iron oxide yellow, magnesium stearate, microcrystalline cellulose, polyethylene glycol, pregelatinized maize starch, titanium dioxide

Questions?

Call toll free 1-800-818-4555 weekdays.

Principal Display Panel

For 180 mg : Label
NDC 62756-545-15
Fexofenadine Hydrochloride Tablets, USP
180 mg
HIVES
(24 Hour)
Reduces HIVES and Relieves ITCHING due to hives
Antihistamine
ORIGINAL PRESCRIPTION STRENGTH
NON-DROWSY
30 Tablets
180 mg each
Actual Size

Principal Display Panel

For 180 mg : Carton
NDC 62756-545-15
Fexofenadine Hydrochloride Tablets, USP
180 mg
HIVES
(24 Hour)
Reduces HIVES and Relieves ITCHING due to hives
Antihistamine
NON-DROWSY
30 Tablets
180 mg each
Actual Size

Principal Display Panel

For 180 mg : Blister Pack
NDC 62756-545-15
ORIGINAL PRESCRIPTION STRENGTH
NON-DROWSY
Fexofenadine Hydrochloride Tablets, USP
180 mg
HIVES
(24 Hour)
Reduces HIVES and Relieves ITCHING due to hives
Antihistamine
5 (1 x 5) Tablets
180 mg each
Actual Size
DO NOT USE IF INDIVIDUAL BLISTER UNIT IS OPEN OR TORN

Principal Display Panel

For 180 mg : Blister Foil
Fexofenadine Hydrochloride Tablets, USP
24 Hour
180 mg
HIVES
Antihistamine
Mfg. by: Sun Pharmaceutical Ind. Ltd., India.